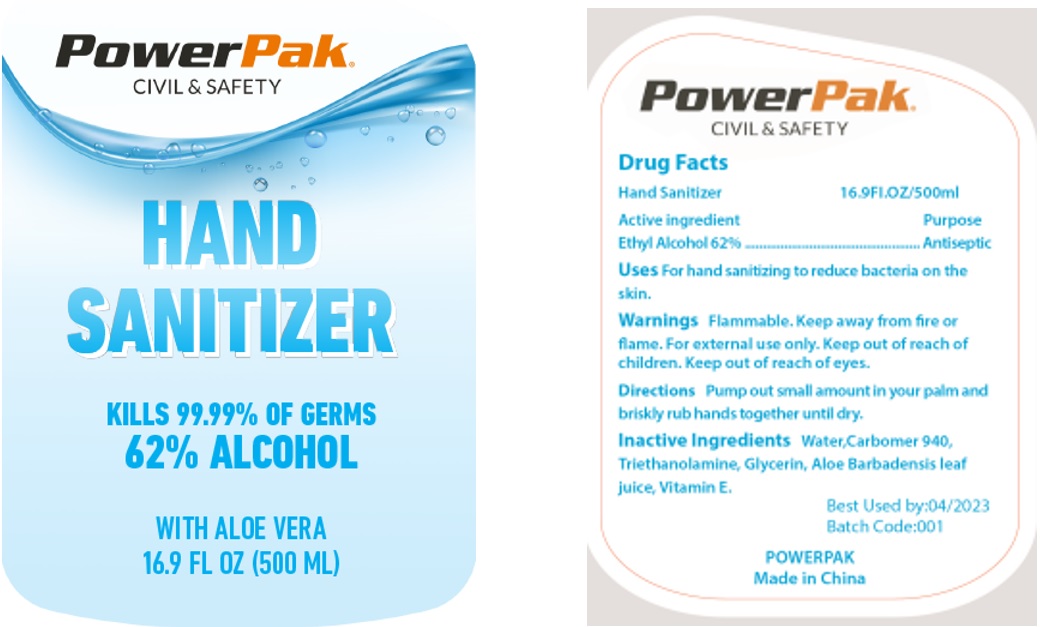 DRUG LABEL: PowerPak Hand Sanitizer
NDC: 75191-920 | Form: GEL
Manufacturer: Powerpak Civil & Safety Llc
Category: otc | Type: HUMAN OTC DRUG LABEL
Date: 20200414

ACTIVE INGREDIENTS: ALCOHOL 62 mL/100 mL
INACTIVE INGREDIENTS: WATER; CARBOMER HOMOPOLYMER TYPE C (ALLYL PENTAERYTHRITOL CROSSLINKED); TROLAMINE; GLYCERIN; ALOE VERA LEAF; .ALPHA.-TOCOPHEROL

PowerPak Civil & Safety Hand Sanitizer

Drug Facts

Hand Sanitizer

Active ingredient

Ethyl Alcohol 62%

Purpose

Antiseptic

INDICATIONS AND USAGE

Uses For hand sanitizing to reduce bacteria on the skin.

WARNINGS

Warnings Flammable. Keep away from fire or flame. For external use only.

Keep out of reach of children. Keep out of reach of eyes.

DOSAGE AND ADMINISTRATION

Directions Pump out small amount in your palm and briskly rub hands together until dry.

INACTIVE INGREDIENT

Inactive Ingredients Water, Carbomer 940, Triethanolamine, Glycerin, Aloe Barbadensis leaf juice, Vitamin E.

KILLS 99.99% OF GERMS

WITH ALOE VERA

Best Used by: 04/2023

Made in China